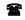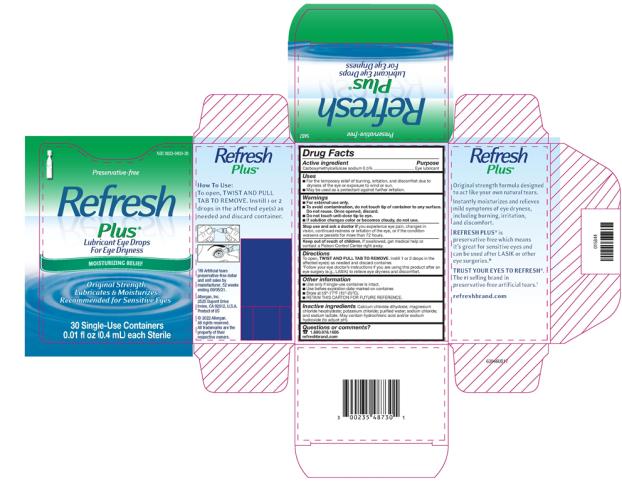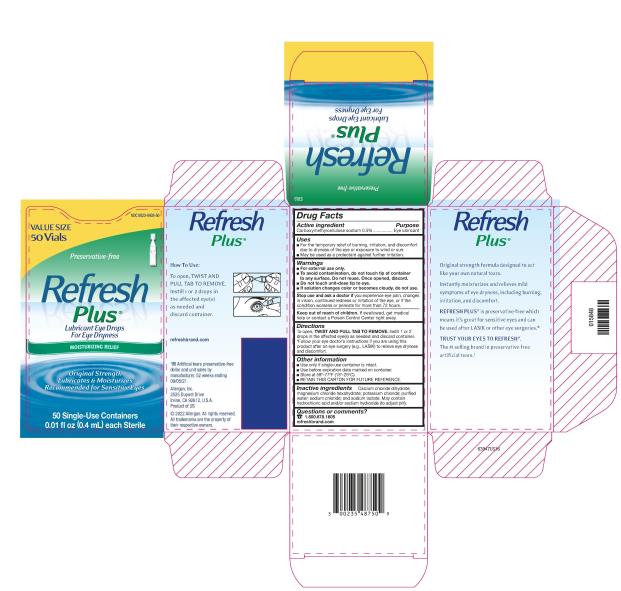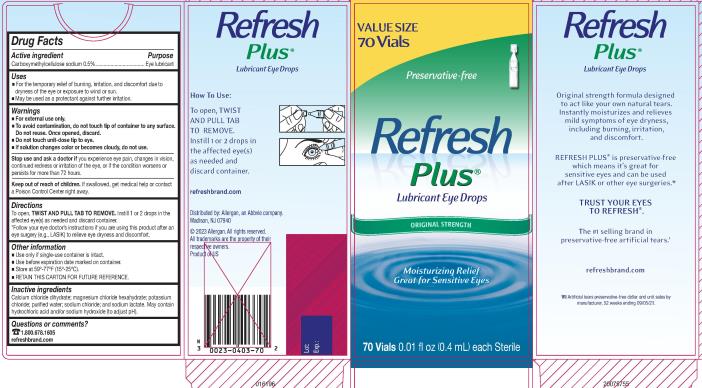 DRUG LABEL: REFRESH PLUS
NDC: 0023-0403 | Form: SOLUTION/ DROPS
Manufacturer: Allergan, Inc.
Category: otc | Type: HUMAN OTC DRUG LABEL
Date: 20220628

ACTIVE INGREDIENTS: CARBOXYMETHYLCELLULOSE SODIUM 5 mg/1 mL
INACTIVE INGREDIENTS: CALCIUM CHLORIDE; MAGNESIUM CHLORIDE; POTASSIUM CHLORIDE; WATER; SODIUM CHLORIDE; SODIUM LACTATE; HYDROCHLORIC ACID; SODIUM HYDROXIDE

REFRESH PLUS® (Preservative-free)
Drug Facts

Active ingredient

Carboxymethylcellulose sodium 0.5%

Purpose

Eye lubricant

Uses

- For the temporary relief of burning, irritation, and discomfort due to dryness of the eye or exposure to wind or sun.
- May be used as a protectant against further irritation.

Warnings

- For external use only.
- To avoid contamination, do not touch tip of container to any surface. Do not reuse. Once opened, discard.
- Do not touch unit-dose tip to eye.
- If solution changes color or becomes cloudy, do not use.

Stop use and ask a doctor if

you experience eye pain, changes in vision, continued redness or irritation of the eye, or if the condition worsens or persists for more than 72 hours.

Keep out of reach of children.

If swallowed, get medical help or contact a Poison Control Center right away.

Directions

To open, TWIST AND PULL TAB TO REMOVE.

Instill 1 or 2 drops in the affected eye(s) as needed and discard container.

*Follow your eye doctor’s instructions if you are using this product after an eye surgery (e.g., LASIK) to relieve eye dryness and discomfort.

Other information

- Use only if single-use container is intact.
- Use before expiration date marked on container.
- Store at 59°-77°F (15°-25°C).
- RETAIN THIS CARTON FOR FUTURE REFERENCE.

Inactive ingredients

Calcium chloride dihydrate; magnesium chloride hexahydrate; potassium chloride; purified water; sodium chloride; and sodium lactate. May contain hydrochloric acid and/or sodium hydroxide (to adjust pH).

Questions or comments?

1.800.678.1605

refreshbrand.com

v1.0DFL0403

PRINCIPAL DISPLAY PANEL

NDC 0023-0403-30
Preservative-free
Refresh
Plus®
Lubricant Eye Drops
For Eye Dryness
MOISTURIZING RELIEF
Original Strength
Lubricates & Moisturizes
Recommended for Sensitive Eyes
30 Single-Use Containers
0.01 fl oz (0.4 mL) each Sterile

PRINCIPAL DISPLAY PANEL

NDC 0023-0403-50
VALUE SIZE
50 Vials
Preservative-free
Refresh
Plus®
Lubricant Eye Drops
For Eye Dryness
MOISTURIZING RELIEF
Original Strength
Lubricates & Moisturizes
Recommended for Sensitive Eyes
50 Single-Use Containers
0.01 fl oz (0.4 mL) each Sterile

PRINCIPAL DISPLAY PANEL

NDC 0023-0403-70
VALUE SIZE
70 Vials
Preservative-free
Refresh
Plus®
Lubricant Eye Drops
ORIGINAL STRENGTH
Moisturizing Relief
Great for Sensitive Eyes
70 Vials 0.01 fl oz (0.4mL) each Sterile